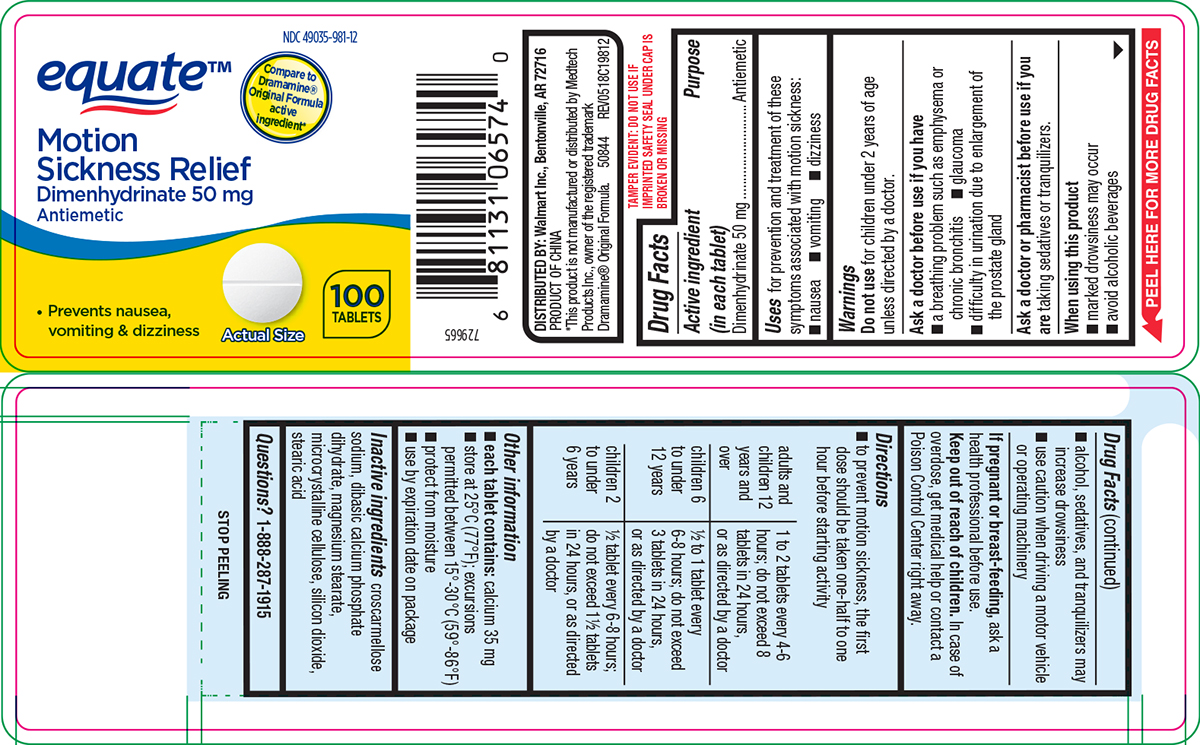 DRUG LABEL: Motion Sickness Relief
NDC: 49035-981 | Form: TABLET
Manufacturer: Wal-Mart Stores Inc
Category: otc | Type: HUMAN OTC DRUG LABEL
Date: 20260202

ACTIVE INGREDIENTS: DIMENHYDRINATE 50 mg/1 1
INACTIVE INGREDIENTS: CROSCARMELLOSE SODIUM; DIBASIC CALCIUM PHOSPHATE DIHYDRATE; MAGNESIUM STEARATE; MICROCRYSTALLINE CELLULOSE; SILICON DIOXIDE; STEARIC ACID

Equate 44-198

Active ingredient (in each tablet)

Dimenhydrinate 50 mg

Purpose

Antiemetic

Uses

for prevention and treatment of these symptoms associated with motion sickness:

- nausea
- vomiting
- dizziness

Warnings

Do not use

for children under 2 years of age unless directed by a doctor.

Ask a doctor before use if you have

- a breathing problem such as emphysema or chronic bronchitis
- glaucoma
- difficulty in urination due to enlargement of the prostate gland

Ask a doctor or pharmacist before use if you are

taking sedatives or tranquilizers.

When using this product

- marked drowsiness may occur
- avoid alcoholic beverages
- alcohol, sedatives, and tranquilizers may increase drowsiness
- use caution when driving a motor vehicle or operating machinery

If pregnant or breast-feeding,

ask a health professional before use.

Keep out of reach of children.

In case of overdose, get medical help or contact a Poison Control Center right away.

Directions

- to prevent motion sickness, the first dose should be taken one-half to one hour before starting activity

adults and children 12 years and over | 1 to 2 tablets every 4-6 hours; do not exceed 8 tablets in 24 hours, or as directed by a doctor
children 6 to under 12 years | 1/2 to 1 tablet every 6-8 hours; do not exceed 3 tablets in 24 hours, or as directed by a doctor
children 2 to under 6 years | 1/2 tablet every 6-8 hours; do not exceed 1 1/2 tablets in 24 hours, or as directed by a doctor

Other information

- each tablet contains: calcium 35 mg
- store at 25ºC (77ºF); excursions permitted between 15º-30ºC (59º-86ºF)
- protect from moisture
- use by expiration date on package

Inactive ingredients

croscarmellose sodium, dibasic calcium phosphate dihydrate, magnesium stearate, microcrystalline cellulose, silicon dioxide, stearic acid

Questions?

1-888-287-1915

Principal Display Panel

NDC 49035-981-12

equate™

Compare to
Dramamine®
Original Formula
active
ingredient*

Motion
Sickness Relief
Dimenhydrinate 50 mg
Antiemetic

• Prevents nausea,
vomiting & dizziness

100
TABLETS

Actual Size

TAMPER EVIDENT: DO NOT USE IF
IMPRINTED SAFETY SEAL UNDER CAP IS
BROKEN OR MISSING

DISTRIBUTED BY: Walmart Inc., Bentonville, AR 72716
PRODUCT OF CHINA
*This product is not manufactured or distributed by Medtech
Products Inc., owner of the registered trademark
Dramamine® Original Formula. 50844 REV0518C19812

Equate 44-198